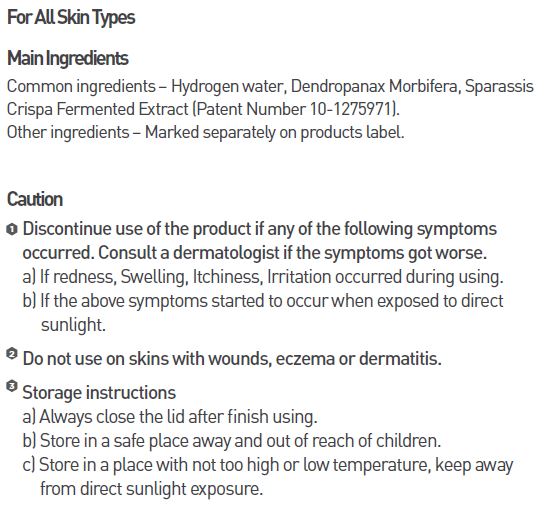 DRUG LABEL: MEDI HYDRO DP
NDC: 70694-0011 | Form: CREAM
Manufacturer: Inc MBG
Category: otc | Type: HUMAN OTC DRUG LABEL
Date: 20190124

ACTIVE INGREDIENTS: GLYCERIN 3 g/100 g
INACTIVE INGREDIENTS: WATER; BUTYLENE GLYCOL

INDICATIONS AND USAGE

Apply enough amount of cream on clean face, gently massage until perfectly absorbed.

Keep out of reach of children.

DOSAGE AND ADMINISTRATION

for external use only

WARNINGS

Discontinue use of the product if any of the following symptoms occurred. Consult a dermatologist if the symptoms got worse.
a) If redness, Swelling, Itchiness, Irritation occurred during using.
b) If the above symptoms started to occur when exposed to direct sunlight.
Do not use on skins with wounds, eczema or dermatitis.

Storage instructions
a) Always close the lid after finish using.
b) Store in a safe place away and out of reach of children.
c) Store in a place with not too high or low temperature, keep awayfrom direct sunlight exposure.

PURPOSE

High moisturization-freshening cream that stays on the skin without sticky feeling

INACTIVE INGREDIENT

water, butylene glycol, niacinamide, etc.

ACTIVE INGREDIENT

glycerin